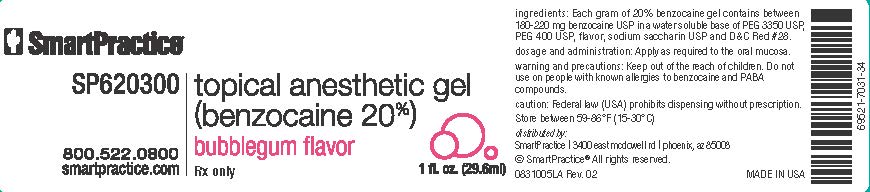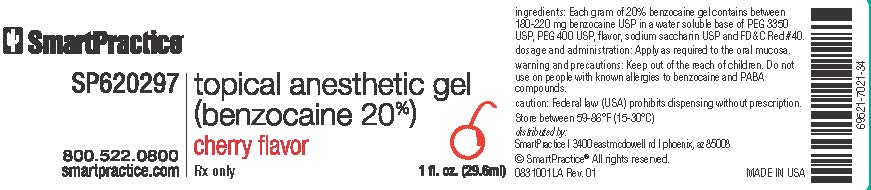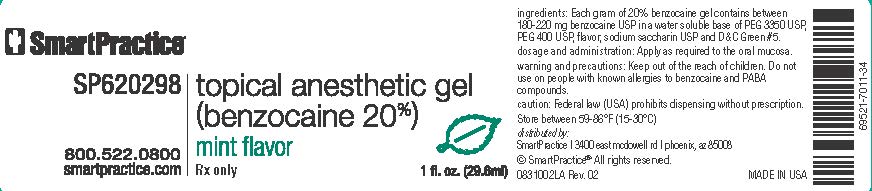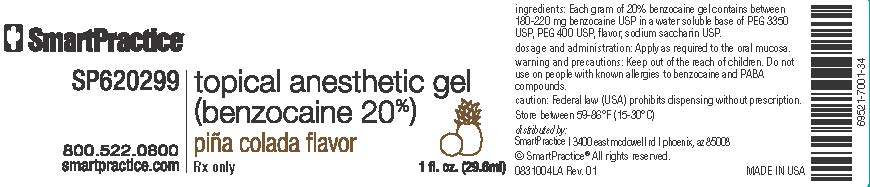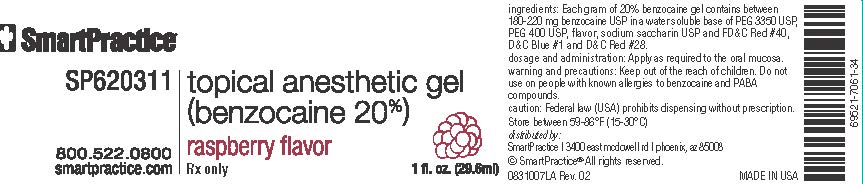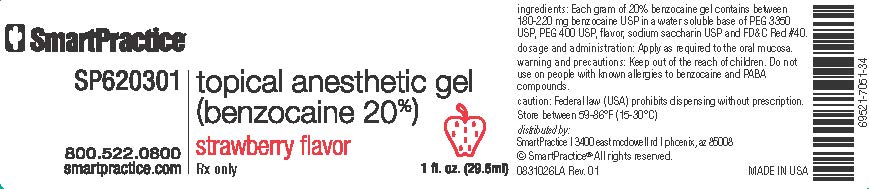 DRUG LABEL: SmartPractice topical anesthetic gel
NDC: 69521-041 | Form: GEL
Manufacturer: SmartHealth, Inc. (DBA SmartPractice)
Category: prescription | Type: HUMAN PRESCRIPTION DRUG LABEL
Date: 20171228

ACTIVE INGREDIENTS: BENZOCAINE 220 mg/1 g
INACTIVE INGREDIENTS: POLYETHYLENE GLYCOL 400; SACCHARIN SODIUM; POLYETHYLENE GLYCOL 3350

SmartPractice topical anesthetic gel

DESCRIPTION

Flavored 20% benzocaine gel or liquid for topical mucosal anesthesia.

INDICATIONS

Indicated as a topical anesthetic for use on oral mucosa prior to local anesthetic injections, scaling and prophylaxis. Also useful to relieve discomfort associated with taking impressions and intra- oral radiographs.

CONTRAINDICATIONS

Should not be used with individuals with a known sensitivity to benzocaine or PABA.

WARNINGS

Keep out of reach of children. For professional dental use only.

PRECAUTIONS

SmartPractice 20% benzocaine gels are supplied in multiple use containers. Take care not to contaminate the bottle by reintroducing a used cotton applicator into the bottle.

DOSAGE AND ADMINISTRATION

1. Each gram of benzocaine gel between 180-220mg benzocaine in a flavored base.

2. Using a new cotton applicator, apply a small amount of gel to the mucosa to achieve topical anesthesia. Do not reintroduce the cotton applicator into the bottle.

3. For topical tissue anesthesia during scaling procedures, dispense a small amount of gel into a dappen dish, then coat the scaler with the product prior to use.

4. Tightly re-cap the jar after each use.

STORAGE

Store between 59°-86°F (15°-30°C). Protect from freezing.

DISTRIBUTED BY

SmartPractice

3400 east mcdowell rd

phoenix, AZ 85008

Made in USA.